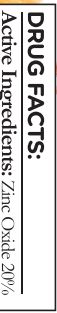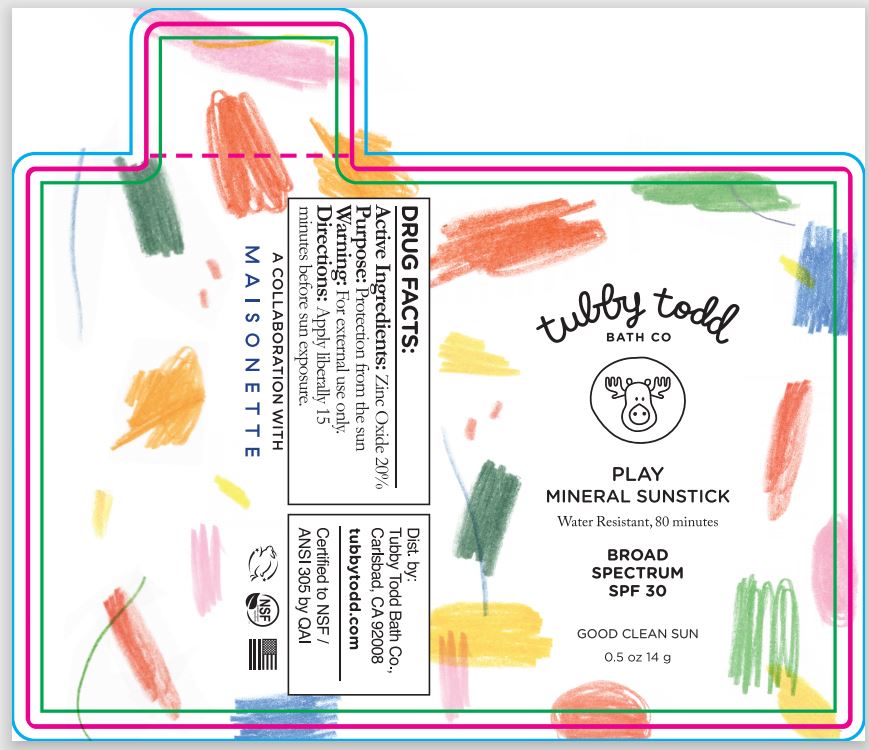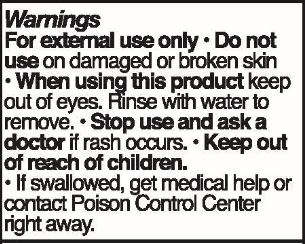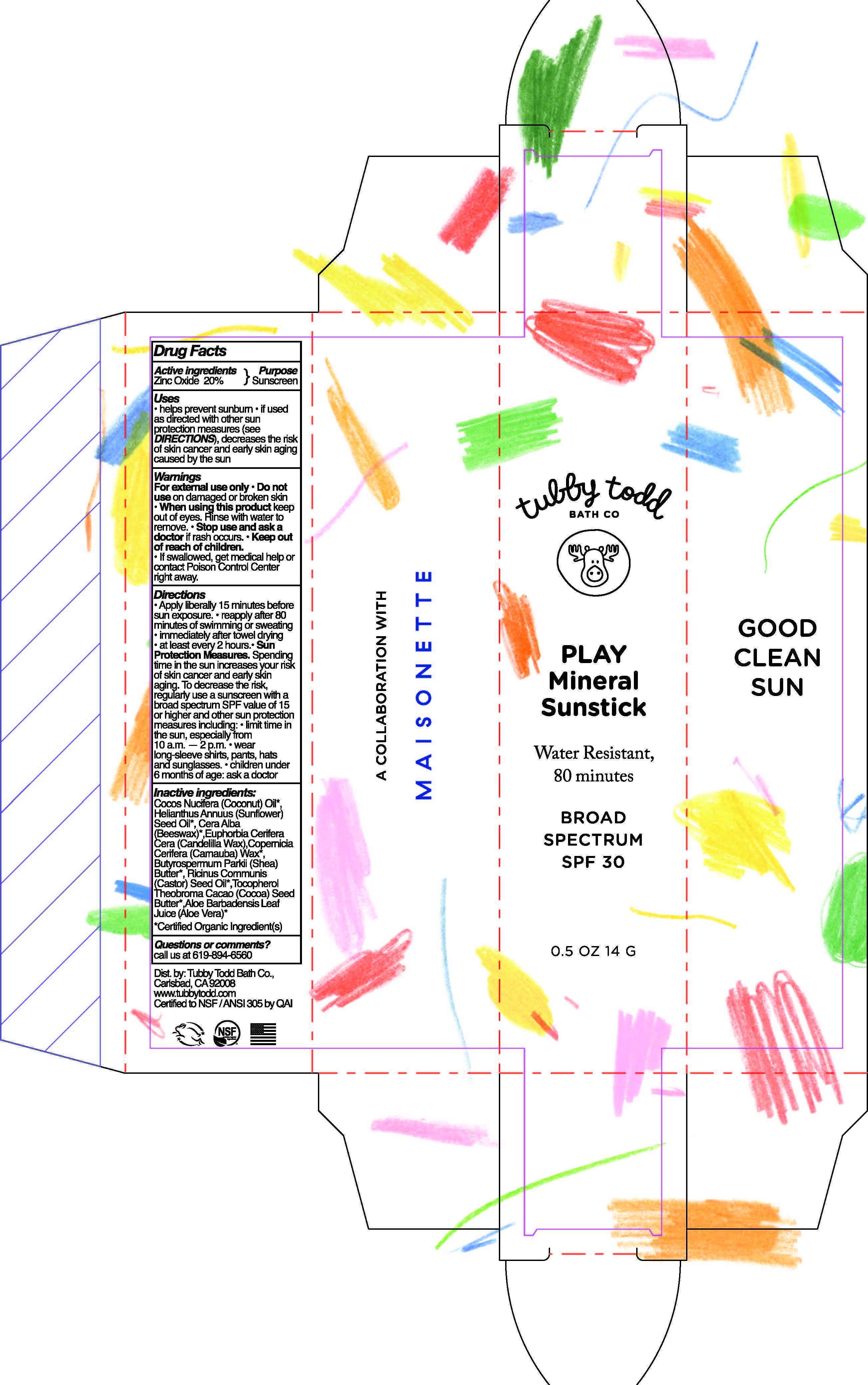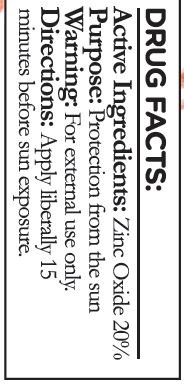 DRUG LABEL: SUNSCREEN
NDC: 62932-250 | Form: STICK
Manufacturer: Private Label Select Ltd CO
Category: otc | Type: HUMAN OTC DRUG LABEL
Date: 20200401

ACTIVE INGREDIENTS: ZINC OXIDE 20 g/100 g
INACTIVE INGREDIENTS: ALOE VERA LEAF; .BETA.-TOCOPHEROL; CANDELILLA WAX; CARNAUBA WAX; COCOA BUTTER; COCONUT OIL; WHITE WAX; SUNFLOWER OIL; SHEA BUTTER; CASTOR OIL

Tubby Todd Play Mineral Sunstick, SPF 30 (Maisonette)